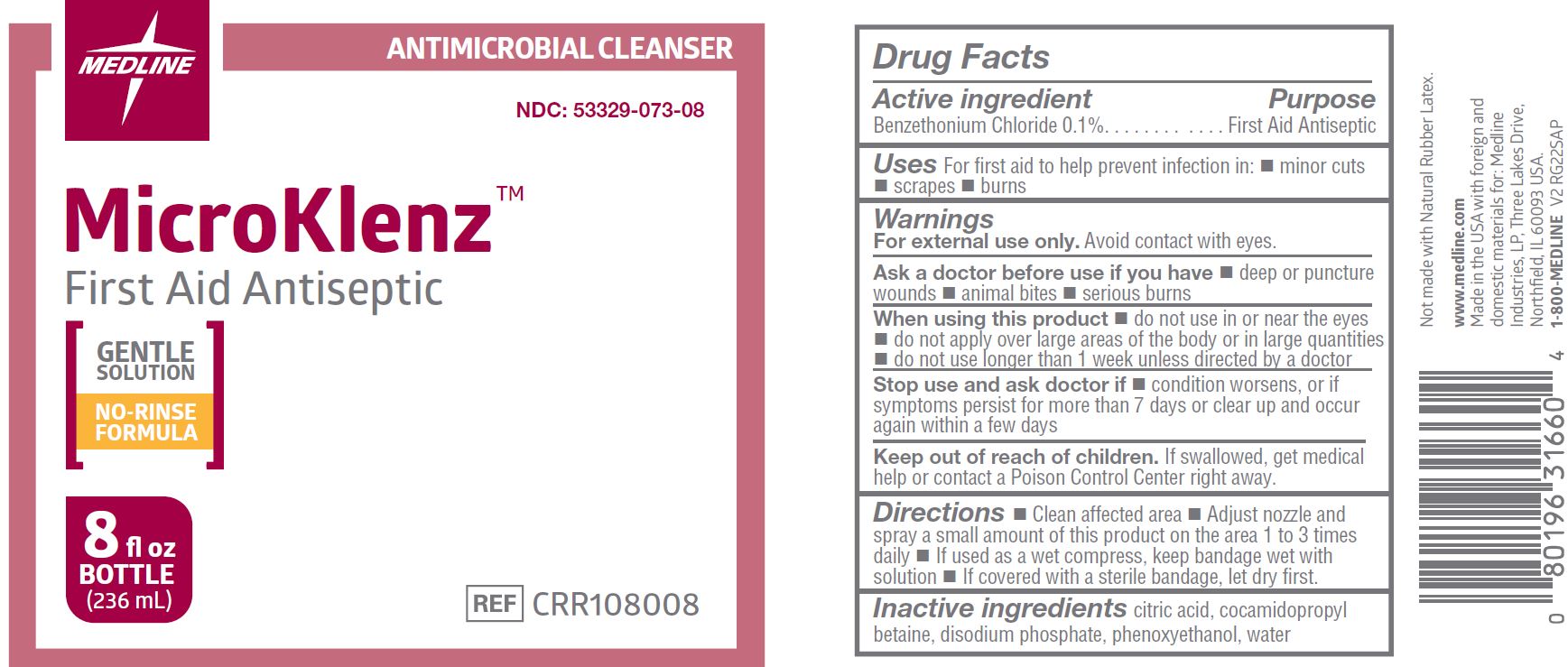 DRUG LABEL: MicroKlenz Antimicrobial
NDC: 53329-073 | Form: LIQUID
Manufacturer: Medline Industries, LP
Category: otc | Type: HUMAN OTC DRUG LABEL
Date: 20241126

ACTIVE INGREDIENTS: BENZETHONIUM CHLORIDE 0.1 mg/100 mL
INACTIVE INGREDIENTS: CITRIC ACID MONOHYDRATE; COCAMIDOPROPYL BETAINE; SODIUM PHOSPHATE, DIBASIC; PHENOXYETHANOL; WATER

073 MicroKlenz First Aid Antiseptic

Active ingredient

Benzethonium Chloride 0.1%

Purpose

First Aid Antiseptic

Uses

For first aid to help prevent infection in:

- minor cuts
- scrapes
- burns

Warnings

For external use only. Avoid contact with eyes.

Ask a doctor before use if you have

- deep or puncture wounds
- animal bites
- serious burns

When using this product

- do not use in or near the eyes
- do not apply over large areas of the body or in large quantities
- do not use longer than 1 week unless directed by a doctor

Stop use and ask a doctor if

- condition worsen or if symptoms persist for more than 7 days or clear up and occur again within a few days.

Keep out of reach of children.

If swallowed, get medical help or contact a Poison Control Center right away.

Directions

- Clean affected area
- Adjust nozzle and spray a small amount of this product on the area 1 to 3 times daily
- If used as a wet compress, keep bandage wet with solution
- If covered with a sterile bandage, let dry first.

Inactive ingredients

citric acid, cocamidopropyl betaine, disodium phosphate, phenoxyethanol, water

Manufacturing Information

Manufactured for:

Medline Industries, LP

Three Lakes Drive, Northfield, IL 60093 USA

Made in the USA with foreign and domestic materials

www.medline.com

1-800-MEDLINE (633-5463)

REF: CRR108008

V2 RG22SAP